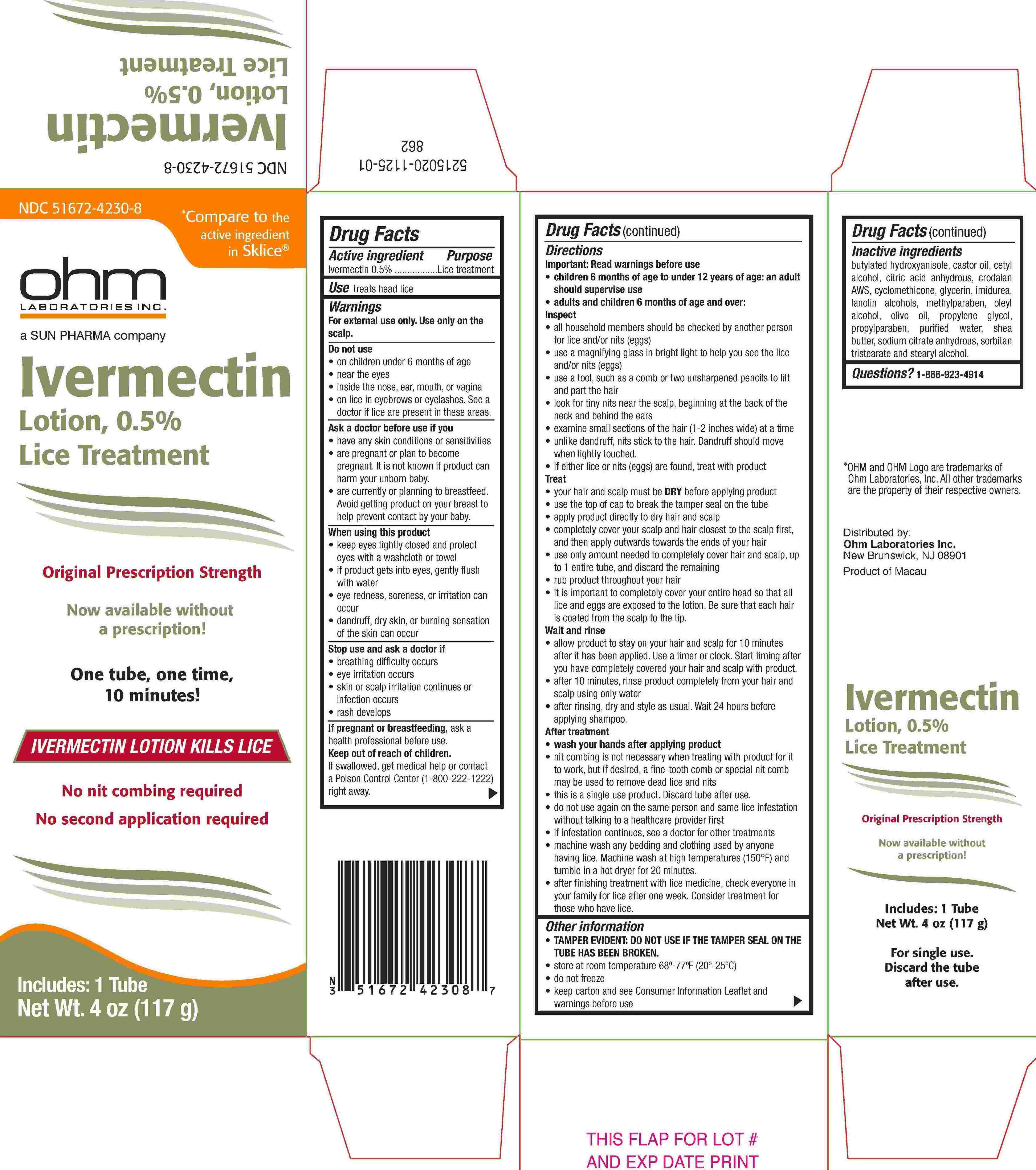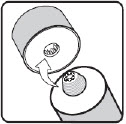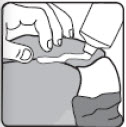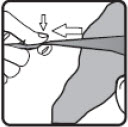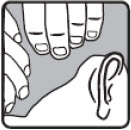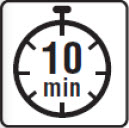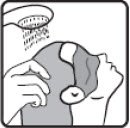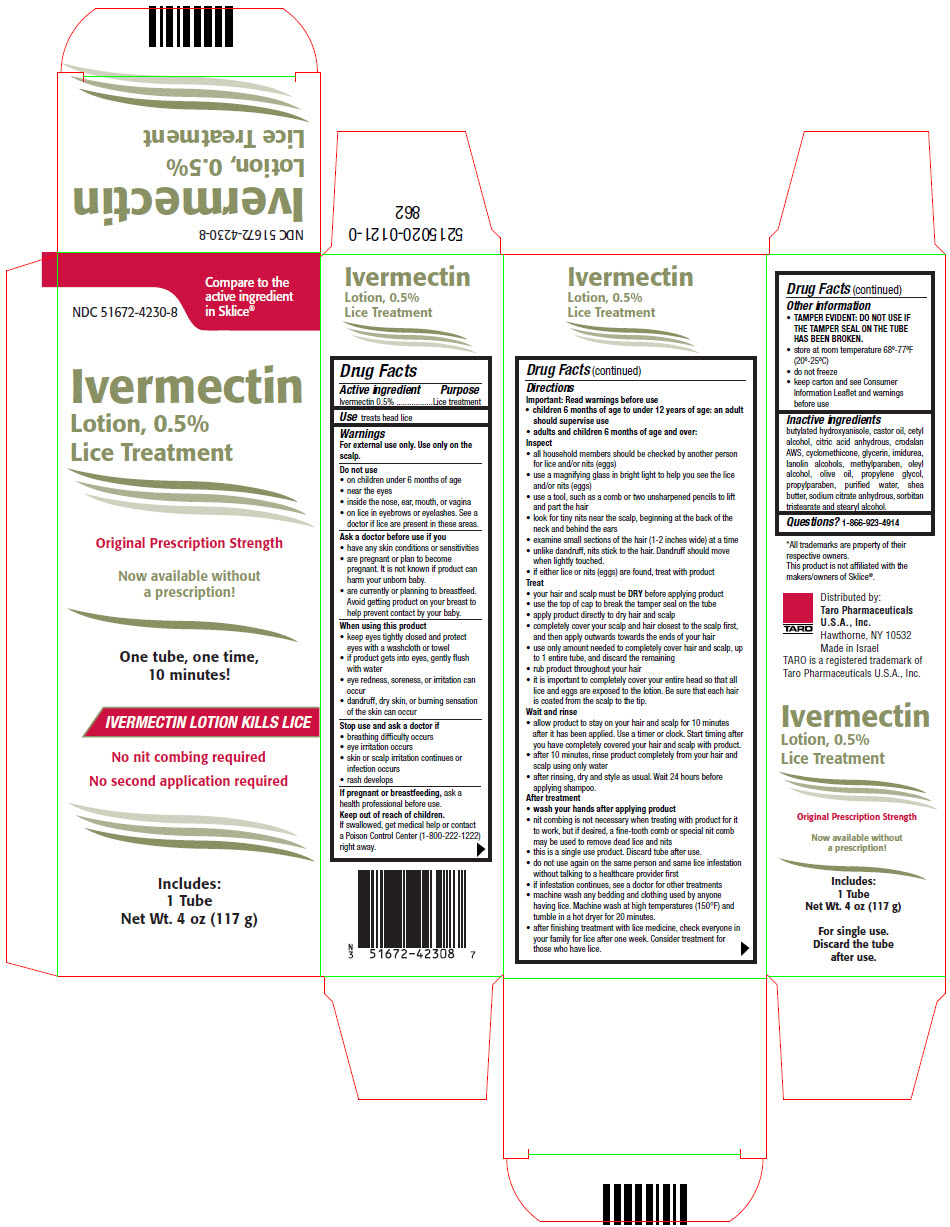 DRUG LABEL: Ivermectin
NDC: 51672-4230 | Form: LOTION
Manufacturer: Sun Pharmaceutical Industries, Inc.
Category: otc | Type: HUMAN OTC DRUG LABEL
Date: 20251222

ACTIVE INGREDIENTS: IVERMECTIN 5 mg/1 g
INACTIVE INGREDIENTS: BUTYLATED HYDROXYANISOLE; CASTOR OIL; CETYL ALCOHOL; ANHYDROUS CITRIC ACID; CYCLOMETHICONE; GLYCERIN; IMIDUREA; LANOLIN ALCOHOLS; METHYLPARABEN; OLEYL ALCOHOL; OLIVE OIL; PROPYLENE GLYCOL; PROPYLPARABEN; WATER; SHEA BUTTER; ANHYDROUS TRISODIUM CITRATE; SORBITAN TRISTEARATE; STEARYL ALCOHOL

Ivermectin

Drug Facts

Active ingredient

Ivermectin 0.5%

Purpose

Lice treatment

Use

treats head lice

Warnings

For external use only. Use only on the scalp.

Do not use

- on children under 6 months of age
- near the eyes
- inside the nose, ear, mouth, or vagina
- on lice in eyebrows or eyelashes. See a doctor if lice are present in these areas.

Ask a doctor before use if you

- have any skin conditions or sensitivities
- are pregnant or plan to become pregnant. It is not known if product can harm your unborn baby.
- are currently or planning to breastfeed. Avoid getting product on your breast to help prevent contact by your baby.

When using this product

- keep eyes tightly closed and protect eyes with a washcloth or towel
- if product gets into eyes, gently flush with water
- eye redness, soreness, or irritation can occur
- dandruff, dry skin, or burning sensation of the skin can occur

Stop use and ask a doctor if

- breathing difficulty occurs
- eye irritation occurs
- skin or scalp irritation continues or infection occurs
- rash develops

PREGNANCY OR BREAST FEEDING

If pregnant or breastfeeding,ask a health professional before use.

Keep out of reach of children.

If swallowed, get medical help or contact a Poison Control Center (1-800-222-1222) right away.

Directions

Important: Read warnings before use

- children 6 months of age to under 12 years of age: an adult should supervise use
- adults and children 6 months of age and over:

Inspect

- all household members should be checked by another person for lice and/or nits (eggs)
- use a magnifying glass in bright light to help you see the lice and/or nits (eggs)
- use a tool, such as a comb or two unsharpened pencils to lift and part the hair
- look for tiny nits near the scalp, beginning at the back of the neck and behind the ears
- examine small sections of the hair (1-2 inches wide) at a time
- unlike dandruff, nits stick to the hair. Dandruff should move when lightly touched.
- if either lice or nits (eggs) are found, treat with product

Treat

- your hair and scalp must be DRYbefore applying product
- use the top of cap to break the tamper seal on the tube
- apply product directly to dry hair and scalp
- completely cover your scalp and hair closest to the scalp first, and then apply outwards towards the ends of your hair
- use only amount needed to completely cover hair and scalp, up to 1 entire tube, and discard the remaining
- rub product throughout your hair
- it is important to completely cover your entire head so that all lice and eggs are exposed to the lotion. Be sure that each hair is coated from the scalp to the tip.

Wait and rinse

- allow product to stay on your hair and scalp for 10 minutes after it has been applied. Use a timer or clock. Start timing after you have completely covered your hair and scalp with product.
- after 10 minutes, rinse product completely from your hair and scalp using only water
- after rinsing, dry and style as usual. Wait 24 hours before applying shampoo.

After treatment

- wash your hands after applying product
- nit combing is not necessary when treating with product for it to work, but if desired, a fine-tooth comb or special nit comb may be used to remove dead lice and nits
- this is a single use product. Discard tube after use.
- do not use again on the same person and same lice infestation without talking to a healthcare provider first
- if infestation continues, see a doctor for other treatments
- machine wash any bedding and clothing used by anyone having lice. Machine wash at high temperatures (150°F) and tumble in a hot dryer for 20 minutes.
- after finishing treatment with lice medicine, check everyone in your family for lice after one week. Consider treatment for those who have lice.

Other information

- TAMPER EVIDENT: DO NOT USE IF THE TAMPER SEAL ON THE TUBE HAS BEEN BROKEN.
- store at room temperature 68º-77ºF (20º-25ºC)
- do not freeze
- keep carton and see Consumer Information Leaflet and warnings before use

Inactive ingredients

butylated hydroxyanisole, castor oil, cetyl alcohol, citric acid anhydrous, crodalan AWS, cyclomethicone, glycerin, imidurea, lanolin alcohols, methylparaben, oleyl alcohol, olive oil, propylene glycol, propylparaben, purified water, shea butter, sodium citrate anhydrous, sorbitan tristearate and stearyl alcohol.

Questions?

1-866-923-4914

Distributed by:
Ohm Laboratories Inc.
New Brunswick, NJ 08901
Made in Israel

Ivermectin Lotion, 0.5% Lice Treatment Lotion

THE FACTS OF LICE

Please read all information before using Ivermectin Lotion.

If you or a member of your household has head lice, don't panic. Keep calm.

Anyone can get head lice – it has nothing to do with cleanliness or poor hygiene.Head lice are treatable and very rarely cause serious health problems.

What are head lice?

- Head lice are small insects that live and feed on the human scalp.
- They may get as big as sesame seeds and are brown.
- Lice do not fly or jump from one person to another. They can only crawl.

What are nits?

- Nits are lice eggs laid on the hair near the scalp. One louse may lay over 100 nits.
- Nits are oval shaped, tiny and greyish-white.
- They are attached to hair with a waterproof glue-like substance that cannot be washed out or blown away.

How do head lice spread?

- Head lice spread easily from close head-to-head or hand-to-head contact with persons who have lice.
- They may also be spread by sharing hats, helmets, scarves, headphones, brushes, combs, bedding and clothing.

How do you know if you have lice?

- Itching is the most common symptom.
- Scratching behind the ears or the back of the neck is a sign that you should check for head lice.
- Scabs or blood spots may be seen.

How do you prevent the spread of lice?

- Avoid direct head-to-head contact with anyone known to have live, crawling lice.
- Do not share combs, brushes, hats, scarves, bandannas, ribbons, barrettes, hair bands, towels, helmets, or other hair-related personal items with anyone else, whether they have lice or not.
- Avoid sleepovers and slumber parties during lice outbreaks.
- Lice can live in bedding, pillows, and carpets that have recently been used by someone with lice.

How do I use Ivermectin Lotion?

Important: Read warnings before use

- Children 6 months of age to under 12 years of age: an adult should supervise use
- Adults and children 6 months of age and over:

Inspect

- All household members should be checked by another person for lice and/or nits (eggs).
- Use a magnifying glass in bright light to help you see the lice and/or nits (eggs).
- Use a tool, such as a comb or two unsharpened pencils to lift and part the hair.
- Look for tiny nits near the scalp, beginning at the back of the neck and behind the ears.
- Examine small sections of the hair (1-2 inches wide) at a time.
- Unlike dandruff, nits stick to the hair. Dandruff should move when lightly touched.
- If either lice or nits (eggs) are found, treat with product.

Treat

- Your hair and scalp must be DRYbefore applying product.

Figure A

- Use the top of cap to break the tamper seal on the tube
  (see Figure A).

- Apply product directly to dry hair and scalp (see Figure B).
- Completely cover your scalp and hair closest to the scalp first, and then apply outwards towards the ends of your hair (see Figure C).
- Use only amount needed to completely cover hair and scalp, up to 1 entire tube, and discard the remaining.
- Rub product throughout your hair (see Figure D).

Figure B

Figure C

Figure D

- It is important to completely cover your entire head so that all lice and eggs are exposed to the lotion. Be sure that each hair is coated from the scalp to the tip.

Wait and rinse

- Allow product to stay on your hair and scalp for 10 minutes after it has been applied. Use a timer or clock. Start timing after you have completely covered your hair and scalp with product (see Figure E).
- After 10 minutes, rinse product completely from your hair and scalp using only water (see Figure F).

Figure E

Figure F

- After rinsing, dry and style as usual. Wait 24 hours before applying shampoo.

After treatment

- Wash your hands after applying product.
- Nit combing is not necessary when treating with product for it to work, but if desired, a fine-tooth comb or special nit comb may be used to remove dead lice and nits.
- This is a single use product. Discard tube after use.
- Do not use again on the same person and same lice infestation without talking to a healthcare provider first.
- If infestation continues, see a doctor for other treatments.
- Machine wash any bedding and clothing used by anyone having lice. Machine wash at high temperatures (150°F) and tumble in a hot dryer for 20 minutes.
- After finishing treatment with lice medicine, check everyone in your family for lice after one week. Consider treatment for those who have lice.

WARNINGS

For external use only. Use only on the scalp.

Do not use

- On children under 6 months of age
- Near the eyes
- Inside the nose, ear, mouth, or vagina
- On lice in eyebrows or eyelashes. See a doctor if lice are present in these areas.

Ask a doctor before use if you

- Have any skin conditions or sensitivities
- Are pregnant or plan to become pregnant. It is not known if product can harm your unborn baby.
- Are currently or planning to breastfeed. Avoid getting product on your breast to help prevent contact by your baby.

When using this product

- Keep eyes tightly closed and protect eyes with a washcloth or towel.
- If product gets into eyes, gently flush with water.
- Eye redness, soreness or irritation can occur.
- Dandruff, dry skin, or burning sensation of the skin can occur.

Stop use and ask a doctor if

- Breathing difficulty occurs
- Eye irritation occurs
- Skin or scalp irritation continues or infection occurs
- Rash develops

If pregnant or breastfeeding,ask a health professional before use.

Keep out of reach of children.If swallowed, get medical help or contact a Poison Control Center (1-800-222-1222) right away.

Questions or comments?Call 1-866-923-4914

Distributed by:
Ohm Laboratories Inc.
New Brunswick, NJ 08901
Made in Israel
Revised: June 2025

PRINCIPAL DISPLAY PANEL - 117 g Tube Carton

Compare to the
active ingredient
in Sklice®

NDC 51672-4230-8

Ivermectin
Lotion, 0.5%
Lice Treatment

Original Prescription Strength

Now available without
a prescription!

One tube, one time,
10 minutes!

IVERMECTIN LOTION KILLS LICE

No nit combing required
No second application required

Includes:
1 Tube
Net Wt. 4 oz (117 g)